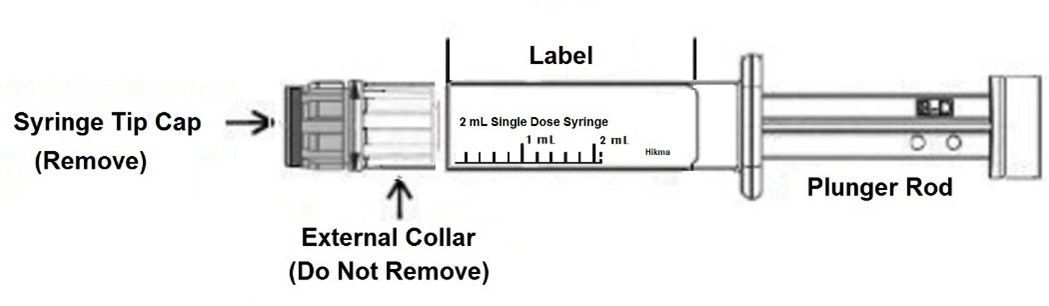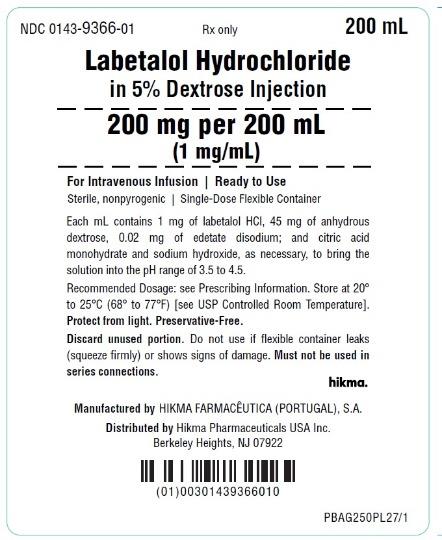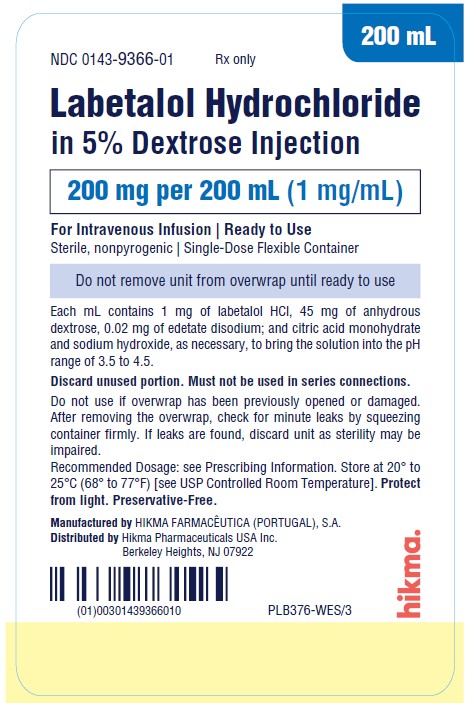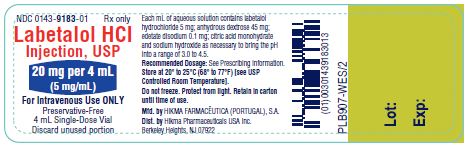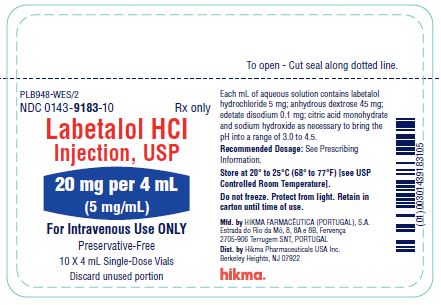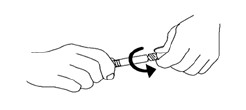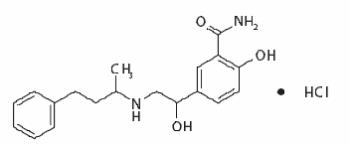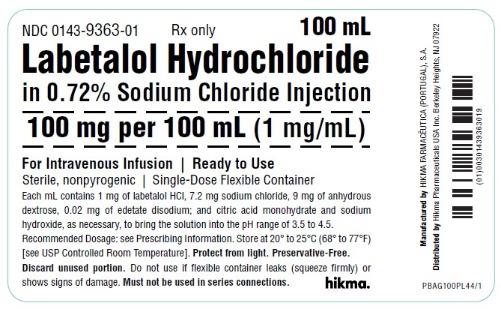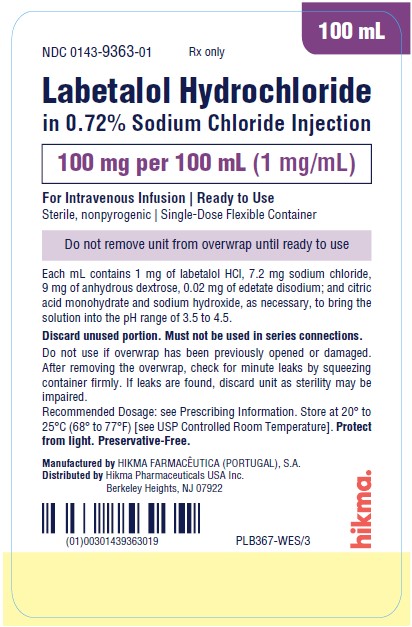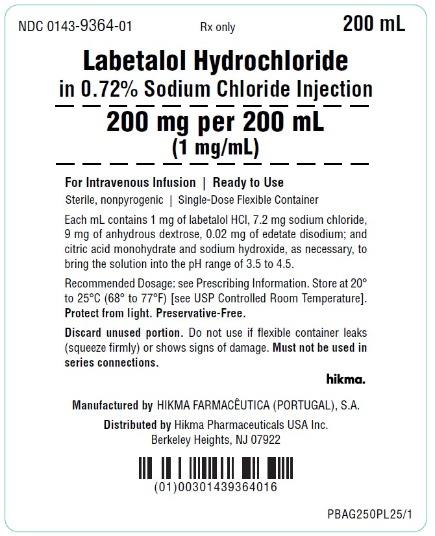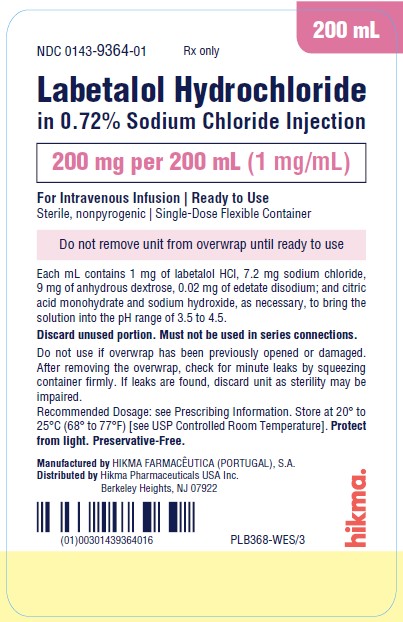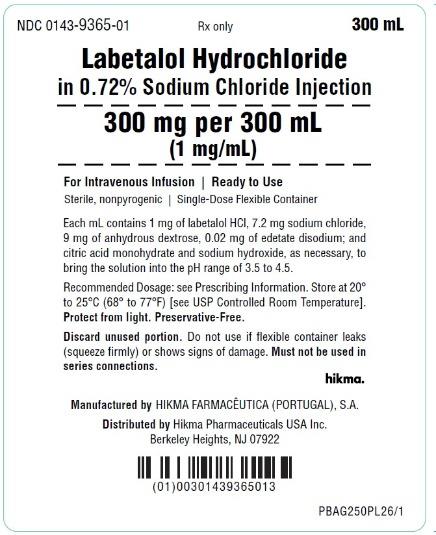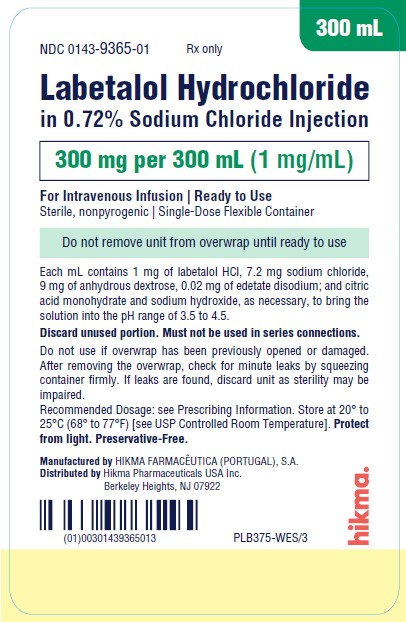 DRUG LABEL: Labetalol HCl in Sodium Chloride
NDC: 0143-9363 | Form: INJECTION
Manufacturer: Hikma Pharmaceuticals USA Inc.
Category: prescription | Type: HUMAN PRESCRIPTION DRUG LABEL
Date: 20251219

ACTIVE INGREDIENTS: LABETALOL HYDROCHLORIDE 1 mg/1 mL
INACTIVE INGREDIENTS: SODIUM CHLORIDE 7.2 mg/1 mL; ANHYDROUS DEXTROSE 9 mg/1 mL; EDETATE DISODIUM 0.02 mg/1 mL; CITRIC ACID MONOHYDRATE; SODIUM HYDROXIDE

HIGHLIGHTS OF PRESCRIBING INFORMATION

These highlights do not include all the information needed to use LABETALOL HYDROCHLORIDE INJECTION safely and effectively. See full prescribing information for LABETALOL HYDROCHLORIDE.
LABETALOL HYDROCHLORIDE IN SODIUM CHLORIDE injection, for intravenous use.
LABETALOL HYDROCHLORIDE IN DEXTROSE injection, for intravenous use.
LABETALOL HYDROCHLORIDE injection, for intravenous use.
Initial U.S. Approval: 1984

1 INDICATIONS AND USAGE

Labetalol Hydrochloride (HCl) is a beta-adrenergic blocker. Labetalol HCl injection is indicated in severe hypertension, to lower blood pressure. (1)

2 DOSAGE AND ADMINISTRATION

Administer Labetalol Hydrochloride in Sodium Chloride Injection or Dextrose Injection as a slow continuous intravenous infusion at a rate of 2 mL/min (2 mg/min). (2.2)

Alternatively, administer Labetalol Hydrochloride Injection in a prefilled syringe or vial at 0.25 mg/kg (up to a maximum of 20 mg) intravenously over 2 minutes. Additional injections of 40 mg or 80 mg can be given at 10-minute intervals. (2.2)

3 DOSAGE FORMS AND STRENGTHS

Labetalol HCl Injection solution:

- 100 mg/100 mL (1 mg/mL) in sodium chloride in a single-dose bag (3)
- 200 mg/200 mL (1 mg/mL) in sodium chloride in a single-dose bag (3)
- 300 mg/300 mL (1 mg/mL) in sodium chloride in a single-dose bag (3)
- 200 mg/200 mL (1 mg/mL) in dextrose in a single-dose bag (3)
- 10 mg/2 mL (5 mg/mL) in a single-dose prefilled syringe (3)
- 20 mg/4 mL (5 mg/mL) in a single-dose vial (3)

4 CONTRAINDICATIONS

- Bronchial asthma (4)
- Overt cardiac failure (4)
- Greater-than-first-degree heart block (4)
- Cardiogenic shock (4)
- Severe bradycardia (4)

5 WARNINGS AND PRECAUTIONS

- Exacerbation of heart failure: Avoid use. (5.3)
- Acute exacerbation of coronary artery disease upon cessation of therapy: Do not abruptly discontinue. (5.4)
- Non-allergic bronchospasm (e.g., chronic bronchitis and emphysema): Avoid since it has not been studied. (5.5)
- Diabetes: May mask symptoms of hypoglycemia and alter glucose levels; monitor (5.6)
- Exacerbation of pheochromocytoma: Paradoxical increases in blood pressure may occur. (5.7)
- Severe hepatocellular injury: Discontinue permanently for liver injury or jaundice (5.8)

6 ADVERSE REACTIONS

Most common adverse events:

- Symptomatic postural hypotension. (6)
- Nausea13%, dizziness 9% (6)

To report SUSPECTED ADVERSE REACTIONS, contact Hikma Pharmaceuticals USA Inc. at 1-877-845-0689, or FDA at 1-800-FDA-1088 or www.fda.gov/medwatch. For product Inquiry call 1-877-845-0689.

7 DRUG INTERACTIONS

- Beta blockers antagonize the bronchodilator effect of beta-receptor agonists. (7.1)
- Increase hypotension may occur with halothane anesthesia. (7.2)
- Nitroglycerin may result in additional hypotensive effects. (7.3)

FULL PRESCRIBING INFORMATION

1 INDICATIONS AND USAGE

Labetalol HCl Injection is indicated in severe hypertension, to lower blood pressure.

2 DOSAGE AND ADMINISTRATION

2.1 General Information

Inspect parenteral drug products for particulate matter and discoloration prior to administration, whenever solution and container permit.

Labetalol HCl in Sodium Chloride Injection and Labetalol HCl in Dextrose Injection:

Labetalol HCl in Sodium Chloride Injection and Labetalol HCl in Dextrose Injection are ready-to-use solutions and do not require further dilution. Check for leaks by squeezing the bag firmly. If leaks are found, discard solution, as sterility may be impaired. Do not add any additional medications to the bag.

Once infusion has started, discard any remaining at 24 hours.

Labetalol HCl Injection in a prefilled syringe or vial:

Labetalol HCl Injection, USP, in a prefilled syringe or vial are ready-to-use solutions that do not require further dilution. The prefilled syringe and vial are intended for single dose. Discard any unused portion.

2.2 Recommended Dosage

Labetalol HCI can be administered by slow continuous intravenous infusion or repeated intravenous injection. Once supine diastolic blood pressure has begun to rise, transition to oral labetalol HCl.

Slow Continuous Intravenous Infusion: Initiate at 2 mg/minute. Monitor blood pressure and adjust the dosage and duration of infusion accordingly.

Repeated Intravenous Injection: Administer 0.25 mg/kg up to 20 mg over 2 minutes. Administer 20 mg to 80 mg over 2 minutes at 10-minute intervals until a desired supine blood pressure is achieved. The maximum effect usually occurs within 5 minutes of each injection.

The safety of doses above 300 mg has not been established.

2.3 Instructions for Use of Labetalol HCl Injection Prefilled Syringe

CAUTION: Glass syringes may malfunction, break or clog when connected to some Needleless Luer Access Devices (NLADs) and needles. The external collar must remain attached to the syringe (See Figure 1). Spontaneous disconnection of this glass syringe from needles and NLADs with leakage of drug product may occur. Assure that the needle or NLAD is securely attached before beginning the injection. Inspect the glass syringe-needle or glass syringe –NLAD connection before and during drug administration.

Figure 1

1. Push plunger rod slightly to break the stopper loose while tip cap is still on.

2. Remove tip cap by twisting it off. (See Figure 2)

Figure 2

3. Connect the syringe to an appropriate injection connection.

4. Depress plunger rod to deliver the required dose.

3 DOSAGE FORMS AND STRENGTHS

Labetalol HCl in Sodium Chloride Injection is a clear, colorless to pale yellow solution available as:

- 100 mg/100 mL (1 mg/mL) in a single-dose bag
- 200 mg/200 mL (1 mg/mL) in a single-dose bag
- 300 mg/300 mL (1 mg/mL) in a single-dose bag

Labetalol HCl in Dextrose Injection is a clear, colorless to pale yellow solution available as:

- 200 mg/200 mL (1 mg/mL) in a single-dose bag

Labetalol HCl Injection is a clear, colorless to pale yellow solution available as:

- 10 mg/2 mL (5 mg/mL) in a single-dose prefilled syringe
- 20 mg/4 mL (5 mg/mL) in a single-dose vial

4 CONTRAINDICATIONS

Labetalol Hydrochloride Injection is contraindicated in patients with:

- Bronchial asthma or obstructive airway disease.
- Severe sinus bradycardia:
- Heart block greater than first degree.
- Cardiogenic shock.
- IV administration of non-dihydropyridine calcium-channel antagonists (e.g., verapamil)
- Hypersensitivity reactions, including anaphylaxis, to labetalol

5 WARNINGS AND PRECAUTIONS

5.1 Hypotension

Symptomatic postural hypotension (incidence, 58%) is likely to occur if patients are tilted or allowed to assume the upright position within 3 hours of receiving labetalol HCl injection. Before permitting any ambulation, establish patient’s ability to tolerate an upright position and observe the patient at the time of first ambulation.

5.2 Bradycardia

Bradycardia, including sinus pause, heart block, severe bradycardia, and cardiac arrest have occurred with the use of beta blockers. Monitor heart rate and rhythm in patients receiving labetalol hydrochloride injection.

5.3 Cardiac Failure

Sympathetic stimulation is a vital component supporting circulatory function in congestive heart failure. Beta-blockade carries a potential hazard of further depressing myocardial contractility and precipitating more severe failure. Avoid labetalol HCl injection in patients with overt congestive heart failure. If patients develop signs or symptoms of heart failure during administration, discontinue labetalol and treat appropriately.

5.4 Ischemic Heart Disease

Abrupt cessation of therapy with beta blocking agents in patients with coronary artery disease, can cause exacerbations of angina pectoris and, in some cases, myocardial infarction has been reported. Therefore, even in the absence of overt angina pectoris, after the discontinuation of labetalol HCl injection observe patients for development or worsening of angina. If patient experiences angina or angina markedly worsens or if acute coronary insufficiency develops, promptly reinstitute labetalol HCl injection and manage as unstable angina.

5.5 Reactive Airway Disease and Nonallergic Bronchospasm

Patients with reactive airways disease should, in general, not receive beta blockers. Labetalol HCl at the usual intravenous therapeutic doses has not been studied in patients with nonallergic bronchospastic disease. In the event of bronchospasm, stop the infusion immediately, and treat as appropriate.

5.6 Hypoglycemia

Beta-blockers may prevent early warning signs of hypoglycemia, such as tachycardia, and increase the risk for severe or prolonged hypoglycemia at any time during treatment, especially in patients with diabetes mellitus or children and patients who are fasting (i.e., surgery, not eating regularly, or are vomiting). If severe hypoglycemia occurs, patients should be instructed to see medical treatment.

5.7 Use in Patients with Pheochromocytoma

Intravenous labetalol has been shown to lower blood pressure and relieve symptoms in patients with pheochromocytoma; higher than usual doses may be required. However, paradoxical hypertensive responses have been reported in a few patients with this tumor; therefore, monitor blood pressure when administering intravenous labetalol HCl to patients with pheochromocytoma.

5.8 Hepatic Injury

Severe hepatocellular injury occurs rarely with labetalol therapy. The hepatic injury is usually reversible, but hepatic necrosis and death have been reported. If the patient develops signs or symptoms of liver injury, institute appropriate treatment and investigate the probable cause. Do not restart labetalol in patients without another explanation for the observed liver injury.

5.9 Use in Patients at Risk of Severe Acute Hypersensitivity Reactions

Patients at risk of anaphylactic reactions may be more reactive to allergen exposure (accidental, diagnostic, or therapeutic). Patients using beta-blockers may be unresponsive to the usual doses of epinephrine used to treat anaphylactic or anaphylactoid reactions. Avoid labetalol HCl injection in patients at high risk of anaphylactic reactions.

5.10 Intraoperative Floppy Iris Syndrome (IFIS)

IFIS has been observed during cataract surgery in some patients treated with alpha-1 blockers (labetalol is an alpha/beta blocker). This variant of small pupil syndrome is characterized by the combination of flaccid iris that billows in response to intraoperative irrigation currents, progressive intraoperative miosis despite preoperative dilation with standard mydriatic drugs, and potential prolapse of the iris toward the phacoemulsification incisions. Inform the patient’s ophthalmologist to be prepared for possible modifications to the surgical technique, such as the utilization of iris hooks, iris dilator rings, or viscoelastic substances.

6 ADVERSE REACTIONS

The following clinically significant adverse reactions are described elsewhere in the labeling:

- Hypotension [see Warnings and Precautions (5.1)]
- Bradycardia [see Warnings and Precautions (5.2)]
- Depression of myocardial contractility in patients with overt congestive heart failure [see Warnings and Precautions (5.3)]
- Aggravation of angina [see Warnings and Precautions (5.4)]
- Significant decline in cardiac output following coronary bypass [see Warnings and Precautions (5.3)]
- Bronchospasm in patients with reactive airway disease [see Warnings and Precautions (5.5)]
- Paradoxical hypertensive responses in patients with pheochromocytoma [see Warnings and Precautions (5.7)]
- Hepatic injury [see Warnings and Precautions (5.8)]
- Acute hypersensitivity reaction [see Warnings and Precautions (5.9)]

6.1 Clinical Trial Experience

Because clinical trials are conducted under widely varying conditions, adverse reaction rates observed in the clinical trials of a drug cannot be directly compared to rates in the clinical trials of another drug and may not reflect the rates observed in practice.

Most adverse effects have been mild and transient and, in controlled trials involving 92 patients, did not require labetalol withdrawal. Symptomatic postural hypotension (incidence, 58%) is likely to occur if patients are tilted or allowed to assume the upright position within 3 hours of receiving labetalol HCl. Moderate hypotension occurred in 1 of 100 patients while supine. Increased sweating was noted in 4 of 100 patients, and flushing occurred in 1 of 100 patients.

The following also were reported with labetalol HCl with the incidence as noted:

Central and Peripheral Nervous Systems

Dizziness in 9%

Paresthesia, most frequently described as tingling of the scalp/skin in 7%

Gastrointestinal System

Nausea in 13%

Vomiting in 4%

Metabolic Disorders

Transient increases in blood urea nitrogen and serum creatinine levels occurred in 8%; these were associated with drops in blood pressure, generally in patients with prior renal insufficiency.

Respiratory System

Bronchospasm

In addition, a number of other less common adverse events have been reported:

Cardiovascular:

Hypotension, and rarely, syncope, bradycardia, heart block.

Liver and Biliary System

Hepatic necrosis, hepatitis, cholestatic jaundice, elevated liver function tests.

Hypersensitivity

Rare reports of hypersensitivity (e.g., rash, urticaria, pruritus, angioedema, dyspnea) and anaphylactoid reactions.

The oculomucocutaneous syndrome associated with the beta blocker practolol has not been reported with labetalol HCl during investigational use and extensive foreign marketing experience.

Clinical Laboratory Tests

Among patients dosed with labetalol tablets, there have been reversible increases of serum transaminases in 4% of patients tested and, more rarely, reversible increases in blood urea.

7 DRUG INTERACTIONS

7.1 Bronchodilators

Labetalol HCl antagonizes the bronchodilatory effect of beta-receptor agonist drugs; therefore, labetalol HCl is contraindicated in patients with bronchial asthma [see Contraindications (4)].

7.2 Anesthesia

Synergism has been shown between halothane anesthesia and intravenously administered labetalol. During controlled hypotensive anesthesia using labetalol in association with halothane, high concentrations (3% or above) of halothane should not be used because the degree of hypotension will be increased and because of the possibility of a large reduction in cardiac output and an increase in central venous pressure.

7.3 Nitroglycerin

Coadministration of labetalol HCl and nitroglycerin will have an additive effect in lowering blood pressure. Additionally, labetalol HCl blunts the reflex tachycardia produced by nitroglycerin. If labetalol is used in patients with angina pectoris on nitroglycerin, monitor patients’ blood pressure and adjust labetalol HCl injection dose as needed. In these patients, avoid initiating labetalol HCl tablets.

7.4 Calcium Channel Blockers

Coadministration of labetalol HCl with non-dihydropyrindine calcium-channel antagonists (e.g., verapamil) is contraindicated [see Contraindications (4)]. Avoid the use of labetalol in patients receiving calcium-channel antagonists.

7.5 Drug/Laboratory Test Interactions

The presence of labetalol metabolites in the urine may result in falsely elevated levels of urinary catecholamines, metanephrine, normetanephrine, and vanillylmandelic acid (VMA) when measured by fluorimetric or photometric methods. In screening patients suspected of having a pheochromocytoma and being treated with labetalol, a specific method, such as a high-performance liquid chromatographic assay with solid phase extraction should be employed in determining levels of catecholamines.

Labetalol has also been reported to produce a false-positive test for amphetamine when screening urine for the presence of drugs using the commercially available assay methods. When patients being treated with labetalol have a positive urine test for amphetamine using these techniques, confirm using more specific methods, such as a gas chromatographic-mass spectrometer technique.

8 USE IN SPECIFIC POPULATIONS

8.1 Pregnancy

Risk Summary

The extensive experience with use of labetalol in pregnant women, based on published interventional and observational studies, has not identified a drug-associated risk for major birth defects, miscarriage, or adverse maternal or fetal outcomes (see Data). Untreated hypertension during pregnancy can lead to serious adverse outcomes for the mother and the fetus (see Clinical Considerations). In animal reproduction studies, oral administration of labetalol to pregnant rats and rabbits during organogenesis at doses up to approximately six and four times the maximum recommended human dose (MRHD), respectively, resulted in no fetal malformations; however, increased fetal resorptions were seen in both species at doses approximating the MRHD (see Data).

In the U.S. general population, the estimated background risk of major birth defects and miscarriage in clinically recognized pregnancies is 2 to 4% and 15 to 20%, respectively. The background risk of major birth defects and miscarriage for the indicated population is unknown.

Clinical Considerations

Disease-Associated Maternal and/or Embryo/Fetal Risk

Hypertension in pregnancy increases the maternal risk for pre-eclampsia, gestational diabetes, premature delivery, and delivery complications (e.g., need for cesarean section, and post-partum hemorrhage). Hypertension increases the fetal risk for intrauterine growth restriction and intrauterine death. Pregnant women with hypertension should be carefully monitored and managed accordingly.

Fetal/Neonatal Adverse Reactions

Labetalol crosses the placenta. Neonates born to mothers who are receiving labetalol during pregnancy, may be at risk for hypotension, bradycardia, hypoglycemia, and respiratory depression. Neonates should be monitored for symptoms of hypotension, bradycardia, hypoglycemia and respiratory depression and manage accordingly.

Data

Human Data

Data from published interventional and observational studies did not demonstrate an association between major congenital malformations and the use of labetalol in pregnancy, however, most studies reported the maternal use of intravenous labetalol occurring after 20 weeks gestation. The published literature has reported inconsistent findings of intrauterine growth retardation, preterm birth and perinatal mortality with maternal use of labetalol during pregnancy; however, these studies have methodological limitations hindering interpretation. These studies cannot definitively establish the absence of risk during pregnancy.

Animal Data

Teratogenic studies were performed with labetalol in rats and rabbits at oral doses up to approximately six and four times the maximum recommended human dose (MRHD), respectively. No reproducible evidence of fetal malformations was observed. Increased fetal resorptions were seen in both species at doses approximating the MRHD.

A teratology study performed with labetalol in rabbits at intravenous doses up to 1.7 times the MRHD revealed no evidence of drug-related harm to the fetus.

Oral administration of labetalol to rats during late gestation through weaning at doses of two to four times the MRHD caused a decrease in neonatal survival.

8.2 Lactation

Risk Summary

Available published data report the presence of labetalol in human milk at low levels. There are no data on the effects on the breastfed infant and on milk production. The developmental and health benefits of breastfeeding should be considered along with the mother's clinical need for labetalol and any potential adverse effects on the breastfed infant from labetalol or from the underlying maternal condition.

8.3 Females and Males of Reproductive Potential

Infertility

Based on the published literature, beta blockers, including labetalol, may cause erectile dysfunction and inhibit sperm motility.

8.4 Pediatric Use

Safety and effectiveness in pediatric patients have not been established.

8.5 Geriatric Use

Some pharmacokinetic studies indicate that the elimination of labetalol is reduced in elderly patients [see Clinical Pharmacology (12.3)]. Geriatric patients treated with labetalol could initiate therapy at the currently recommended dose of 2 mg/minute by continuous intravenous infusion; however, lower maintenance dosages are generally required for elderly patients than nonelderly patients. Monitor blood pressure and adjust the dosage and duration of infusion accordingly until the desired response is obtained [see Dosage and Administration (2)].

10 OVERDOSAGE

10.1 Signs and Symptoms of Overdose

Overdosage with labetalol HCl causes excessive hypotension that is posture sensitive and, sometimes, excessive bradycardia. Patients should be placed supine and their legs raised if necessary, to improve the blood supply to the brain. Treat symptoms of overdose with standard supportive care. If overdosage with labetalol HCl follows oral ingestion, gastric lavage or pharmacologically induced emesis (using syrup of ipecac) may be useful for removal of the drug shortly after ingestion.

Neither hemodialysis nor peritoneal dialysis removes a significant amount of labetalol from the general circulation (<1%).

The oral LD50 value of labetalol HCl in the mouse is approximately 600 mg/kg and in the rat is greater than 2 g/kg. The intravenous LD50 in these species is 50 to 60 mg/kg.

11 DESCRIPTION

Labetalol HCl in Sodium Chloride Injection, Labetalol HCl in Dextrose Injection and Labetalol Hydrochloride Injection, USP contain labetalol HCl an adrenergic receptor blocking agent that has both selective alpha1-adrenergic and nonselective beta-adrenergic receptor blocking actions. Labetalol hydrochloride (HCl) is a racemate chemically designated as 5-[1-Hydroxy-2-[(1-methyl-3-phenylpropyl)amino]ethyl]-salicylamide monohydrochloride and it has the following structural formula:

Labetalol HCl is a white or off-white crystalline powder, soluble in water. Labetalol HCl has the molecular formula C19H24N2O3•HCl and a molecular weight of 364.87. It has two asymmetric centers and therefore exists as a molecular complex of two diastereoisomeric pairs.

Labetalol HCl in Sodium Chloride Injection and Labetalol HCl in Dextrose Injection are two preservative-free, ready- to use formulations of labetalol. Labetalol HCl in Sodium Chloride Injection and Labetalol HCl in Dextrose Injection are clear, colorless to pale yellow, aqueous, sterile, isotonic solution for intravenous injection.

Each milliliter of Labetalol HCl in Sodium Chloride Injection contains 1 mg of labetalol HCl, 7.2 mg sodium chloride, 9 mg of anhydrous dextrose, 0.02 mg of edetate disodium; and citric acid monohydrate and sodium hydroxide, as necessary, to bring the solution into the pH range of 3.5 to 4.5.

Each milliliter of Labetalol HCl in Dextrose Injection contains 1 mg of labetalol HCl, 45 mg of anhydrous dextrose, 0.02 mg of edetate disodium; and citric acid monohydrate and sodium hydroxide, as necessary, to bring the solution into the pH range of 3.5 to 4.5.

Labetalol Hydrochloride Injection prefilled syringe and vial are two preservative-free, ready-to use formulations of labetalol. Labetalol Hydrochloride Injection is a clear, colorless to pale yellow, aqueous, sterile, isotonic solution for intravenous injection.

Each milliliter of Labetalol Hydrochloride Injection, USP, contains 5 mg of labetalol HCI, 45 mg of anhydrous dextrose, 0.1 mg of edetate disodium, and citric acid monohydrate and sodium hydroxide, as necessary, to bring the solution into the pH range of 3.0 to 4.5.

12 CLINICAL PHARMACOLOGY

12.1 Mechanism of Action

Labetalol has both competitive alpha1-adrenergic blocking and competitive beta-adrenergic blocking activity. In man, the ratio of alpha- to beta-blockade has been estimated to be approximately 1:7 following intravenous administration. Beta2-agonist activity has been demonstrated in animals with minimal beta1-agonist activity detected.

12.2 Pharmacodynamics

In a clinical pharmacologic study in severe hypertensives, an initial 0.25 mg/kg injection of labetalol HCl administered to patients in the supine position decreased blood pressure by an average of 11/7 mmHg. Additional injections of 0.5 mg/kg at 15-minute intervals up to a total cumulative dose of 1.75 mg/kg of labetalol HCl caused further dose-related decreases in blood pressure. Some patients required cumulative doses of up to 3.25 mg/kg. The maximal effect of each dose level occurred within 5 minutes. Following discontinuation of intravenous treatment with labetalol HCl, the blood pressure rose gradually and progressively, approaching pretreatment baseline values within an average of 16 to 18 hours in the majority of patients.

Similar results were obtained in the treatment of patients with severe hypertension who required urgent blood pressure reduction with an initial dose of 20 mg (which corresponds to 0.25 mg/kg for an 80 kg patient) followed by additional doses of either 40 mg or 80 mg at 10 minute intervals to achieve the desired effect, or up to a cumulative dose of 300 mg.

Labetalol HCl administered as a continuous intravenous infusion, with a mean dose of 136 mg (27 mg to 300 mg) over a period of 2 to 3 hours (mean of 2 hours and 39 minutes), lowered the blood pressure by an average of 60/35 mmHg.

12.3 Pharmacokinetics

Distribution

Labetalol has been shown to cross the placental barrier in humans. Only negligible amounts of the drug crossed the blood-brain barrier in animal studies. Labetalol is approximately 50% protein bound. Neither hemodialysis nor peritoneal dialysis removes a significant amount of labetalol from the systemic circulation (<1%).

Elimination

Following intravenous infusion of labetalol, the elimination half-life is about 5.5 hours and the total body clearance is approximately 33 mL/min/kg. Steady-state plasma levels of labetalol during repetitive dosing are reached following 22 to 28 hours of continuous infusion.

Metabolism

The metabolism of labetalol is mainly through conjugation to glucuronide metabolites.

Excretion

Approximately 55% to 60% of a dose appears in the urine as conjugates or unchanged labetalol within the first 24 hours of dosing. The metabolites are present in plasma and are excreted in the urine and, via the bile, into the feces.

Specific Populations

Patients with Renal or Hepatic Impairment

In patients with decreased hepatic or renal function, the elimination half-life of labetalol is not altered.

Geriatric Patients

Some pharmacokinetic studies indicate that the elimination of labetalol is reduced in elderly patients.

13 NONCLINICAL TOXICOLOGY

13.1 Carcinogenesis, Mutagenesis, Impairment of Fertility

Long-term oral dosing studies with labetalol for 18 months in mice and for 2 years in rats showed no evidence of carcinogenesis. Studies with labetalol using dominant lethal assays in rats and mice and exposing microorganisms according to modified Ames tests showed no evidence of mutagenesis.

16 HOW SUPPLIED/STORAGE AND HANDLING

16.1 How Supplied

Labetalol HCl in Sodium Chloride Injection and Labetalol HCl in Dextrose Injection are preservative-free, clear, colorless to pale yellow sterile solutions that are available in a single-dose single-port bag with an aluminum overwrap. The container closure is not made with natural rubber latex. It is available in the following presentations:

Product | Strength | Package | NDC Number
Labetalol HCl in Sodium Chloride Injection | 100 mg/100 mL (1 mg/mL) preservative-free | 1 single-dose bag | 0143-9363-01
Labetalol HCl in Sodium Chloride Injection | 100 mg/100 mL (1 mg/mL) preservative-free | Box of 10 bags | 0143-9363-10
Labetalol HCl in Sodium Chloride Injection | 200 mg/200 mL (1 mg/mL) preservative-free | 1 single-dose bag | 0143-9364-01
Labetalol HCl in Sodium Chloride Injection | 200 mg/200 mL (1 mg/mL) preservative-free | Box of 10 bags | 0143-9364-10
Labetalol HCl in Sodium Chloride Injection | 300 mg/300 mL (1 mg/mL) preservative-free | 1 single-dose bag | 0143-9365-01
Labetalol HCl in Sodium Chloride Injection | 300 mg/300 mL (1 mg/mL) preservative-free | Box of 10 bags | 0143-9365-10
Labetalol HCl in Dextrose Injection | 200 mg/200 mL (1 mg/mL) preservative-free | 1 single-dose bag | 0143-9366-01
Labetalol HCl in Dextrose Injection | 200 mg/200 mL (1 mg/mL) preservative-free | Box of 10 bags | 0143-9366-10

Labetalol Hydrochloride Injection, USP is a preservative-free, clear, colorless to pale yellow sterile solution that is available in a single-dose prefilled syringe or vial. It is available in the following presentations:

Product | Strength | Package | NDC Number
Labetalol Hydrochloride Injection, USP | 10 mg/2 mL (5 mg/mL) preservative-free | 1 single-dose prefilled syringe | 0641-6252-01
Labetalol Hydrochloride Injection, USP | 10 mg/2 mL (5 mg/mL) preservative-free | Carton of 10 prefilled syringes | 0641-6252-10
Labetalol Hydrochloride Injection, USP | 20 mg/4 mL (5 mg/mL) preservative-free | 1 single-dose vial | 0143-9183-01
Labetalol Hydrochloride Injection, USP | 20 mg/4 mL (5 mg/mL) preservative-free | Carton of 10 vials | 0143-9183-10

16.2 Storage

Store at 20°C to 25°C (68°F to 77°F) with excursions permitted between 15°C to 30° C (59°F to 86° F) [see USP Controlled Room Temperature]. DO NOT FREEZE. PROTECT FROM LIGHT.

Labetalol HCl in Sodium Chloride Injection and Labetalol HCl in Dextrose Injection: Do not remove from overwrap until ready to use.

Labetalol Hydrochloride Injection, USP, prefilled syringe and vial: Retain in carton until time of use.

17 PATIENT COUNSELING INFORMATION

- Advise patients to remain supine and to proceed gradually in becoming ambulatory during and immediately following infusion (for up to 3 hours) of labetalol HCl injection.
- Inform patient to notify their healthcare provider if they experience symptoms of hypotension.
- Advise about the risk of hypoglycemia when Labetalol is given to patients who are fasting or who are vomiting. Inform patient to notify their healthcare provider if they experience symptoms of hypoglycemia. [See Warnings and Precautions (5.6)].

Distributed by

Hikma Pharmaceuticals USA Inc.

Berkeley Heights, NJ 07922

PIN539-WES/6

Revised: August 2024

PRINCIPAL DISPLAY PANEL

NDC 0143-9363-01 Rx only 100 mL
Labetalol Hydrochloride
in 0.72% Sodium Chloride Injection
100 mg per 100 mL (1 mg/mL)
For Intravenous Infusion Ready to Use
Sterile, nonpyrogenic Single-Dose Flexible Container

NDC 0143-9363-01 Rx only 100 mL
Labetalol Hydrochloride
in 0.72% Sodium Chloride Injection
100 mg per 100 mL (1 mg/mL)
For Intravenous Infusion Ready to Use
Sterile, nonpyrogenic Single-Dose Flexible Container

PRINCIPAL DISPLAY PANEL

NDC 0143-9364-01 Rx only 200 mL
Labetalol Hydrochloride
in 0.72% Sodium Chloride Injection
200 mg per 200 mL
(1 mg/mL)
For Intravenous Infusion Ready to Use
Sterile, nonpyrogenic Single-Dose Flexible Container

NDC 0143-9364-01 Rx only 200 mL
Labetalol Hydrochloride
in 0.72% Sodium Chloride Injection
200 mg per 200 mL (1 mg/mL)
For Intravenous Infusion Ready to Use
Sterile, nonpyrogenic Single-Dose Flexible Container

PRINCIPAL DISPLAY PANEL

NDC 0143-9365-01 Rx only 300 mL
Labetalol Hydrochloride
in 0.72% Sodium Chloride Injection
300 mg per 300 mL
(1 mg/mL)
For Intravenous Infusion Ready to Use
Sterile, nonpyrogenic Single-Dose Flexible Container

NDC 0143-9365-01 Rx only 300 mL
Labetalol Hydrochloride
in 0.72% Sodium Chloride Injection
300 mg per 300 mL (1 mg/mL)
For Intravenous Infusion Ready to Use
Sterile, nonpyrogenic Single-Dose Flexible Container

PRINCIPAL DISPLAY PANEL

NDC 0143-9366-01 Rx only 200 mL
Labetalol Hydrochloride
in 5% Dextrose Injection
200 mg per 200 mL
(1 mg/mL)
For Intravenous Infusion Ready to Use
Sterile, nonpyrogenic Single-Dose Flexible Container

NDC 0143-9366-01 Rx only 200 mL
Labetalol Hydrochloride
in 5% Dextrose Injection
200 mg per 200 mL (1 mg/mL)
For Intravenous Infusion Ready to Use
Sterile, nonpyrogenic Single-Dose Flexible Container

PRINCIPAL DISPLAY PANEL

NDC 0143-9183-01Rx only

Labetalol HCI Injection, USP

20 mg per 4 mL

(5 mg/mL)

For Intravenous Use ONLY

Preservative-Free

4 mL Single-Dose Vial

Discard unused portion

NDC 0143-9183-10 Rx only

Labetalol HCI Injection, USP

20 mg per 4 mL

(5 mg/mL)

For Intravenous Use ONLY

Preservative-Free

10 X 4 mL Single-Dose Vials

Discard unused portion